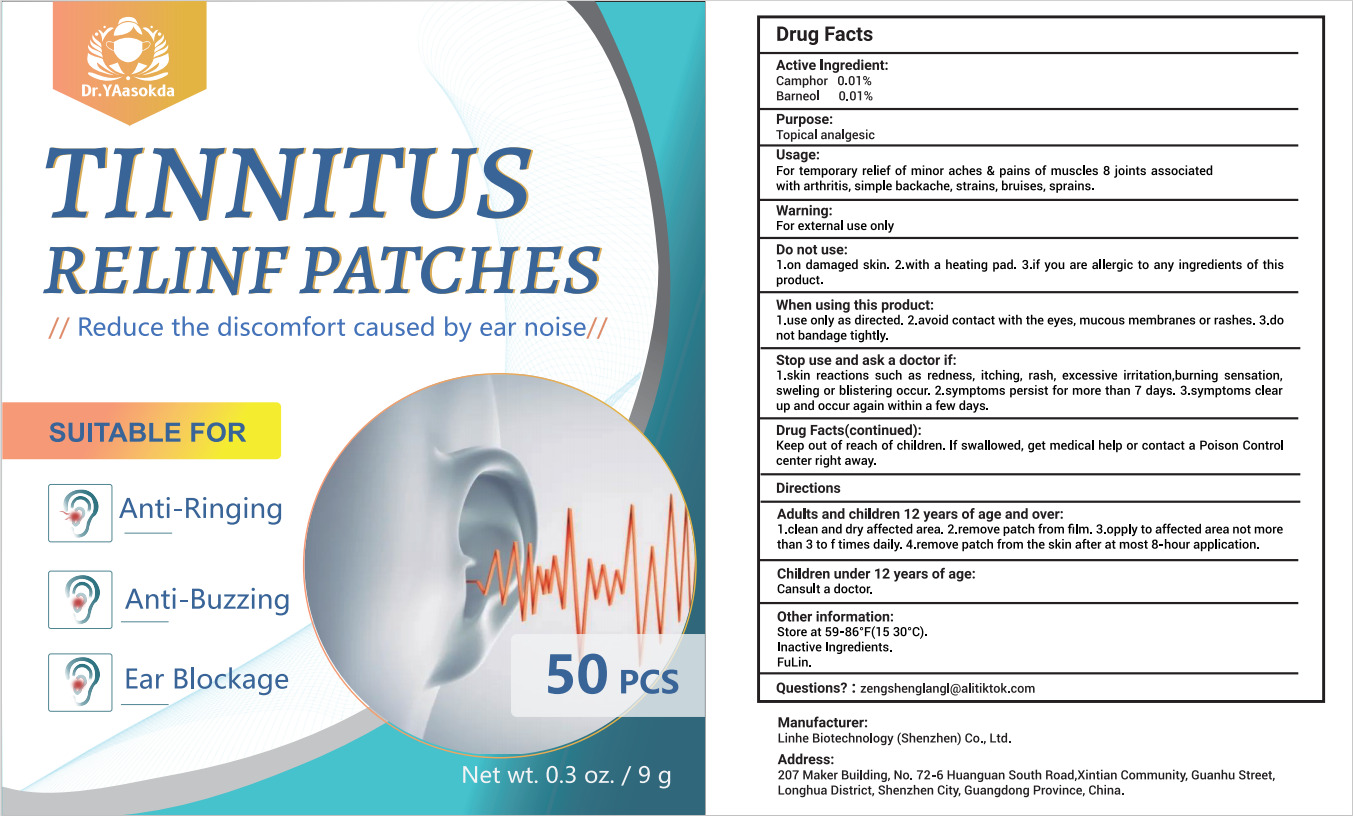 DRUG LABEL: TINNITUS RELINF PATCHES
NDC: 84575-002 | Form: PATCH
Manufacturer: Linhe Biotechnology (Shenzhen) Co., Ltd
Category: otc | Type: HUMAN OTC DRUG LABEL
Date: 20240801

ACTIVE INGREDIENTS: BORNEOL 0.1 g/9 g; CAMPHOR, (-)- 0.1 g/9 g
INACTIVE INGREDIENTS: FU LING

TINNITUS RELINF PATCHES

ACTIVE INGREDIENT

Camphor 0.01%

Borneol 0.01%

PURPOSE

Topical analgesic

INDICATIONS AND USAGE

For temporary relief of minor aches & pains of muscles 8 joints associated with arthritis, simple backache, strains, bruises, sprains

WARNINGS

For external use only

DO NOT USE

1.on damaged skin. 2.with a heating pad. 3.if you are allergic to any ingredients of this product.

WHEN USING

1.use only as directed. 2.avoid contact with the eyes, mucous membranes or rashes. 3.do not bandage tightly.

STOP USE

1.skin reactions such as redness, itching, rash, excessive irritation,burning sensation,sweling or blistering occur, 2.symptoms persist for more than 7 days. 3.symptoms clear up and occur again within a few days.

KEEP OUT OF REACH OF CHILDREN

lf swallowed, get medical help or contact a Poison Control center right away.

DOSAGE AND ADMINISTRATION

Adults and children 12 years of age and over:

1.clean and dry affected area. 2.remove patch from film. 3.opply to affected area not morethan 3 to f times daily. 4.remove patch from the skin after at most 8-hour application.

Children under 12 years of age:

Cansult a doctor.

INACTIVE INGREDIENT

Fu Ling